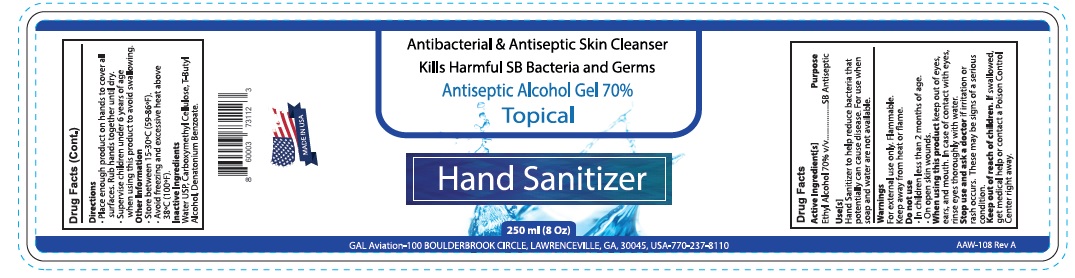 DRUG LABEL: Hand Sanitizer
NDC: 79352-001 | Form: GEL
Manufacturer: AEROQUEST, INC
Category: otc | Type: HUMAN OTC DRUG LABEL
Date: 20200623

ACTIVE INGREDIENTS: ALCOHOL 70 mL/100 mL
INACTIVE INGREDIENTS: CARBOXYMETHYLCELLULOSE SODIUM, UNSPECIFIED FORM; TERT-BUTYL ALCOHOL; DENATONIUM BENZOATE ANHYDROUS; WATER

Active Ingredient

Ethyl Alcohol 70% v/v.

Uses

- antiseptic skin cleanser
- antibacterial cleanser
- kills harmful bacteria and germs

Warnings

For external use only.

Flammability warning: Keep away from open flame and sources of heat.

When using this product avoid contact with eyes. In case of contact with eyes, rinse eyes thoroughly with water.
Stop use and ask a doctor if irritation develops.

Keep out of reach of children. If swallowed, call a poison control center or get medical help right away.

Directions

- Adults and children over 2 years: For occasional and personal domestic use.
- Supervise children when they use this product.
- Rub thoroughty into hands for at least 30 seconds. Allow to dry.

Inactive ingredients

Aqua, Carboxymethyl cellulose, tert - butyl alcohol, denatonium benzoate